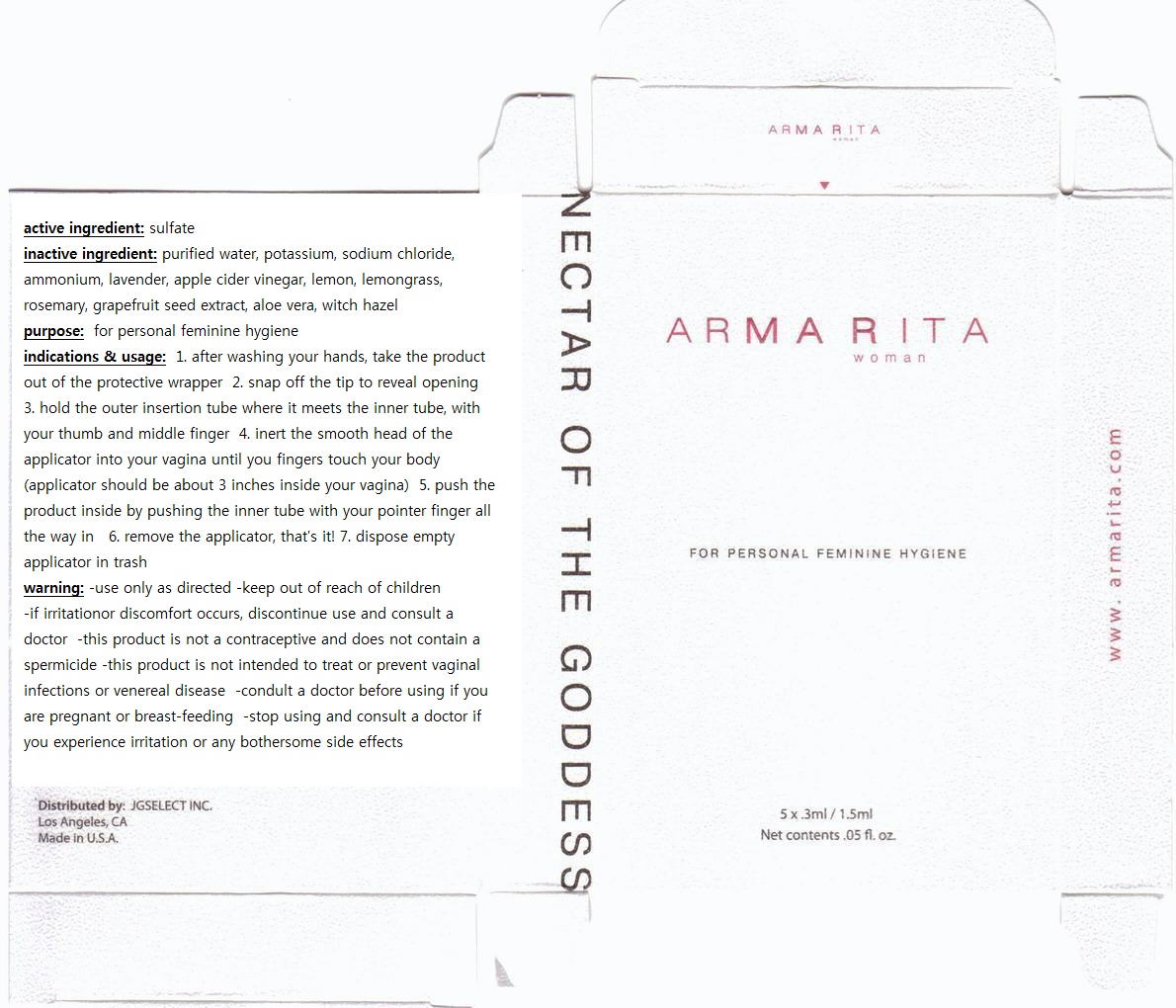 DRUG LABEL: Armarita
                
NDC: 53028-1001 | Form: LIQUID
Manufacturer: JG Select Inc
Category: otc | Type: HUMAN OTC DRUG LABEL
Date: 20120802

ACTIVE INGREDIENTS: Sulfur 0.12 mg/3 mL
INACTIVE INGREDIENTS: SODIUM; CHLORIDE ION; AMMONIA; LAVANDULA ANGUSTIFOLIA FLOWER; APPLE CIDER VINEGAR; LEMON; WEST INDIAN LEMONGRASS OIL; ROSEMARY; CITRUS PARADISI SEED; ALOE VERA LEAF; WITCH HAZEL; POTASSIUM

Drug Facts

active ingredient: sulfate

INACTIVE INGREDIENT

purified water, potassium, sodium chloride, ammonium, lavender, apple cider vinegar, lemon, lemongrass, rosemary, grapefruit seed extract, aloe vera, witch hazel

PURPOSE

for personal feminine hygiene

keep out of reach of the children

INDICATIONS AND USAGE

1. after washing your hands, take the product out of the protective wrapper
2. snap off the tip to reveal opening
3. hold the outer insertion tube where it meets the inner tube, with your thumb and middle finger
4. inert the smooth head of the applicator into your vagina until you fingers touch your body (applicator should be about 3 inches inside your vagina)
5. push the product inside by pushing the inner tube with your pointer finger all the way in
6. remove the applicator, that's it!
7. dispose empty applicator in trash

WARNINGS

- use only as directed
- keep out of reach of children
- if irritationor discomfort occurs, discontinue use and consult a doctor.
- this product is not a contraceptive and does not contain a spermicide
- this product is not intended to treat or prevent vaginal infections or venereal disease
- condult a doctor before using if you are pregnant or breast-feeding
- stop using and consult a doctor if you experience irritation or any bothersome side effects

DOSAGE AND ADMINISTRATION

- inert the smooth head of the applicator into your vagina until you fingers touch your body (applicator should be about 3 inches inside your vagina)